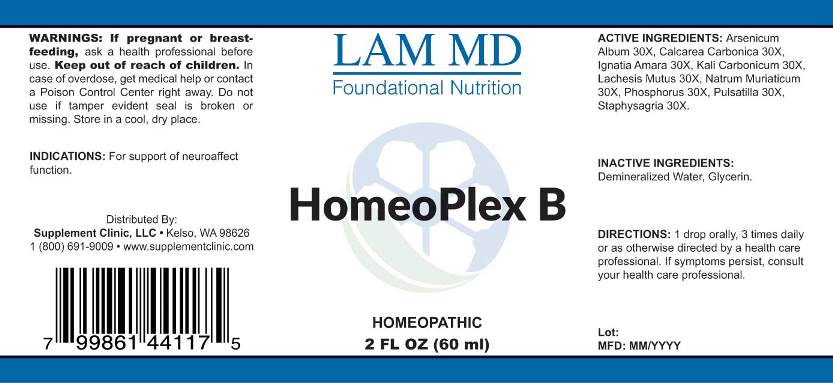 DRUG LABEL: Homeoplex B
NDC: 71781-0002 | Form: LIQUID
Manufacturer: Supplement Clinic, LLC.
Category: homeopathic | Type: HUMAN OTC DRUG LABEL
Date: 20171031

ACTIVE INGREDIENTS: ARSENIC TRIOXIDE 30 [hp_X]/1 mL; OYSTER SHELL CALCIUM CARBONATE, CRUDE 30 [hp_X]/1 mL; STRYCHNOS IGNATII SEED 30 [hp_X]/1 mL; POTASSIUM CARBONATE 30 [hp_X]/1 mL; LACHESIS MUTA VENOM 30 [hp_X]/1 mL; SODIUM CHLORIDE 30 [hp_X]/1 mL; PHOSPHORUS 30 [hp_X]/1 mL; PULSATILLA VULGARIS 30 [hp_X]/1 mL; DELPHINIUM STAPHISAGRIA SEED 30 [hp_X]/1 mL
INACTIVE INGREDIENTS: WATER; GLYCERIN

Drug Facts:

ACTIVE INGREDIENTS:

Arsenicum Album 30X, Calcarea Carbonica 30X, Ignatia Amara 30X, Kali Carbonicum 30X, Lachesis Mutus 30X, Natrum Muriaticum 30X, Phosphorus 30X, Pulsatilla 30X, Staphysagria 30X.

INDICATIONS:

For support of neuroaffect function.

WARNINGS:

If pregnant or breast-feeding, ask a health professional before use.
Keep out of reach of children. In case of overdose, get medical help or contact a Poison Control Center right away.
Do not use if tamper evident seal is broken or missing.
Store in cool, dry place.

Keep out of reach of children. In case of overdose, get medical help or contact a Poison Control Center right away.

DIRECTIONS:

1 drop orally, 3 times daily or as otherwise directed by a health care professional. If symptoms persist, consult your health care professional.

INDICATIONS:

For support of neuroaffect function.

INACTIVE INGREDIENTS:

Demineralized Water, Glycerin

QUESTIONS:

Distributed By:
Supplement Clinic, LLC. • Kelso, WA 98626
1(800)691-9009 • www.supplementclinic.com

PACKAGE LABEL DISPLAY:

LAM MD
Foundational Nutrition
HomeoPlex B
HOMEOPATHIC
2 FL OZ (60 ml)